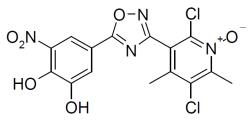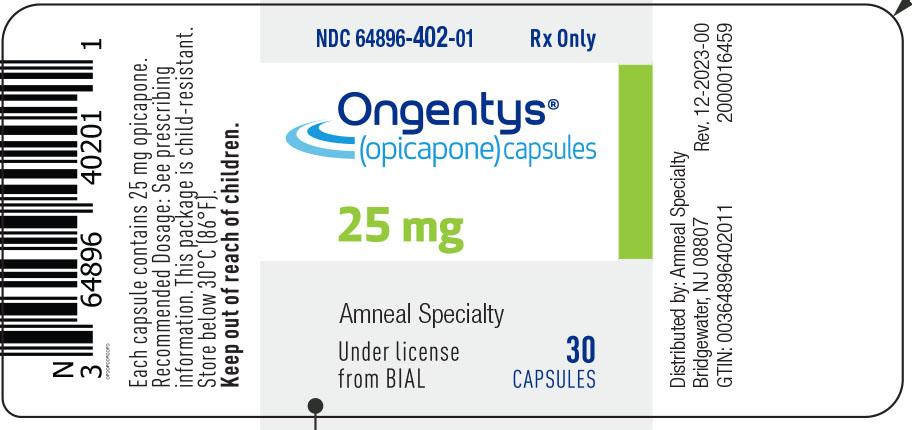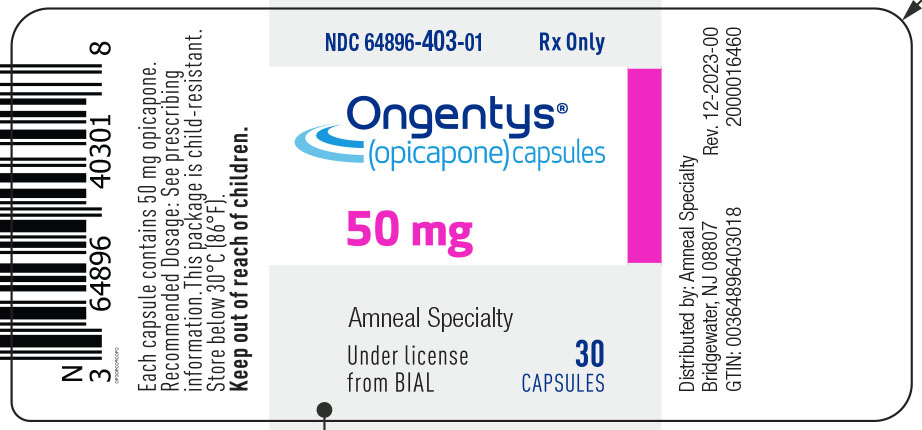 DRUG LABEL: ONGENTYS
NDC: 64896-402 | Form: CAPSULE
Manufacturer: Amneal Pharmaceuticals LLC
Category: prescription | Type: HUMAN PRESCRIPTION DRUG LABEL
Date: 20251015

ACTIVE INGREDIENTS: OPICAPONE 25 mg/1 1
INACTIVE INGREDIENTS: STARCH, CORN; LACTOSE, UNSPECIFIED FORM; SODIUM STARCH GLYCOLATE TYPE A POTATO; MAGNESIUM STEARATE; GELATIN; TITANIUM DIOXIDE; FD&C RED NO. 3; FD&C BLUE NO. 2

HIGHLIGHTS OF PRESCRIBING INFORMATION

These highlights do not include all the information needed to use ONGENTYS® safely and effectively. See full prescribing information for ONGENTYS®.
ONGENTYS (opicapone) capsules, for oral use
Initial U.S. Approval: 2020

1 INDICATIONS AND USAGE

ONGENTYS is a catechol-O-methyltransferase (COMT) inhibitor indicated as adjunctive treatment to levodopa/carbidopa in patients with Parkinson’s disease (PD) experiencing “off” episodes. (1)

2 DOSAGE AND ADMINISTRATION

- The recommended dosage is 50 mg administered orally once daily at bedtime. (2.1)
- Patients should not eat food for 1 hour before and for at least 1 hour after intake of ONGENTYS. (2.1)
- The recommended dosage in patients with moderate hepatic impairment is 25 mg orally once daily at bedtime; avoid use in patients with severe hepatic impairment. (2.2)

3 DOSAGE FORMS AND STRENGTHS

Capsules: 25 mg and 50 mg. (3)

4 CONTRAINDICATIONS

- Concomitant use of non-selective monoamine oxidase (MAO) inhibitors. (4)
- History of pheochromocytoma, paraganglioma, or other catecholamine secreting neoplasms. (4)

5 WARNINGS AND PRECAUTIONS

- Cardiovascular Effects with Concomitant Use of Drugs Metabolized by Catechol-O-Methyltransferase (COMT): May cause arrhythmias, increased heart rate, and excessive changes in blood pressure. Monitor patients when treated concomitantly with products metabolized by COMT. (4, 5.1)
- Falling Asleep During Activities of Daily Living: Advise patients prior to treatment. (5.2)
- Hypotension/Syncope: If occurs, consider discontinuing ONGENTYS or adjusting dosage of other medications that can lower blood pressure. (5.3)
- Dyskinesia: May cause or exacerbate dyskinesia; consider levodopa or dopaminergic medication dose reduction. (5.4)
- Hallucinations and Psychosis: Consider stopping ONGENTYS if occurs. (5.5)
- Impulse Control/Compulsive Disorders: Consider stopping ONGENTYS if occurs. (5.6)
- Withdrawal-Emergent Hyperpyrexia and Confusion: When discontinuing ONGENTYS, monitor patients and consider adjustment of other dopaminergic therapies as needed. (5.7)

6 ADVERSE REACTIONS

Most common adverse reactions (≥4% and > placebo): dyskinesia, constipation, blood creatine kinase increased, hypotension/syncope, and weight decreased. (6.1)

To report SUSPECTED ADVERSE REACTIONS, contact Amneal Pharmaceuticals at 1-877-835-5472 or FDA at 1-800-FDA-1088 or www.fda.gov/medwatch.

8 USE IN SPECIFIC POPULATIONS

- Pregnancy: Based on animal data, may cause fetal harm (8.1)
- Avoid use in patients with end-stage renal disease. (8.6)

FULL PRESCRIBING INFORMATION

1 INDICATIONS AND USAGE

ONGENTYS is indicated as adjunctive treatment to levodopa/carbidopa in patients with Parkinson’s disease (PD) experiencing “off” episodes.

2 DOSAGE AND ADMINISTRATION

2.1 Dosing and Administration Information

The recommended dosage of ONGENTYS is 50 mg administered orally once daily at bedtime. Patients should not eat food for 1 hour before and for at least 1 hour after intake of ONGENTYS [see Clinical Pharmacology (12.3)].

2.2 Dosage Recommendations for Patients with Hepatic Impairment

In patients with moderate hepatic impairment (Child-Pugh B), the recommended dose of ONGENTYS is 25 mg orally once daily at bedtime [see Use in Specific Populations (8.7), Clinical Pharmacology (12.3)].

Avoid use of ONGENTYS in patients with severe (Child-Pugh C) hepatic impairment [see Use in Specific Populations (8.7), Clinical Pharmacology (12.3)].

2.3 Discontinuation and Missed Dose

When discontinuing ONGENTYS, monitor patients and consider adjustment of other dopaminergic therapies as needed. If a dose of ONGENTYS is missed, the next dose should be taken at the scheduled time the next day.

3 DOSAGE FORMS AND STRENGTHS

ONGENTYS capsules are available in the following strengths:

- 50 mg capsules with a dark blue opaque cap and dark pink opaque body; axially printed with “OPC” over “50” in white ink, on both the cap and body.
- 25 mg capsules with a light blue opaque cap and light pink opaque body; axially printed with “OPC” over “25” in blue ink, on both the cap and body.

4 CONTRAINDICATIONS

ONGENTYS is contraindicated in patients with:

- Concomitant use of non-selective monoamine oxidase (MAO) inhibitors [see Drug Interactions (7.1)].
- Pheochromocytoma, paraganglioma, or other catecholamine secreting neoplasms.

5 WARNINGS AND PRECAUTIONS

5.1 Cardiovascular Effects with Concomitant Use of Drugs Metabolized by Catechol-O-Methyltransferase (COMT)

Possible arrhythmias, increased heart rate, and excessive changes in blood pressure may occur with concomitant use of ONGENTYS and drugs metabolized by COMT (e.g., isoproterenol, epinephrine, norepinephrine, dopamine, and dobutamine), regardless of the route of administration (including inhalation). Monitor patients treated concomitantly with ONGENTYS and drugs metabolized by COMT [see Contraindications (4), Drug Interactions (7.1, 7.2)].

5.2 Falling Asleep During Activities of Daily Living and Somnolence

Patients treated with dopaminergic medications and medications that increase levodopa exposure, including ONGENTYS, have reported falling asleep while engaged in activities of daily living, including the operation of motor vehicles, which sometimes has resulted in accidents. Patients may not perceive warning signs, such as excessive drowsiness, or they may report feeling alert immediately prior to the event.

Before initiating treatment with ONGENTYS, advise patients of the potential to develop drowsiness and specifically ask about factors that may increase the risk for somnolence with dopaminergic therapy, such as concomitant sedating medications or the presence of a sleep disorder. If a patient develops daytime sleepiness or episodes of falling asleep during activities that require full attention (e.g., driving a motor vehicle, conversations, eating), consider discontinuing ONGENTYS or adjusting other dopaminergic or sedating medications. If a decision is made to continue ONGENTYS, patients should be advised not to drive and to avoid other potentially dangerous activities.

5.3 Hypotension/Syncope

In Study 1 and Study 2 [see Clinical Studies (14)], hypotension (orthostatic and non-orthostatic), syncope, and presyncope occurred in 5% of patients treated with ONGENTYS 50 mg compared to 1% of patients who received placebo. Monitor patients for hypotension (orthostatic and non-orthostatic) and advise patients about the risk for syncope and presyncope. If these adverse reactions occur, consider discontinuing ONGENTYS or adjusting the dosage of other medications that can lower blood pressure.

5.4 Dyskinesia

ONGENTYS potentiates the effects of levodopa [see Clinical Pharmacology (12.3)] and may cause dyskinesia or exacerbate pre-existing dyskinesia.

In controlled clinical trials (Study 1 and Study 2) [see Clinical Studies (14)], dyskinesia occurred in 20% of patients treated with ONGENTYS 50 mg compared to 6% of patients who received placebo. Dyskinesia was also the most common adverse reaction leading to discontinuation of ONGENTYS [see Adverse Reactions (6.1)].

Reducing the patient’s daily levodopa dosage or the dosage of another dopaminergic drug may mitigate dyskinesia that occurs during treatment with ONGENTYS.

5.5 Hallucinations and Psychosis

In Study 1 and Study 2, hallucinations (hallucinations, auditory hallucinations, visual hallucinations, mixed hallucinations) occurred in 3% of patients treated with ONGENTYS 50 mg compared to 1% of patients who received placebo. Delusions, agitation, or aggressive behavior occurred in 1% of patients treated with ONGENTYS 50 mg, and in no patient who received placebo. Consider stopping ONGENTYS if hallucinations or psychotic-like behaviors occur.

Patients with a major psychotic disorder should ordinarily not be treated with ONGENTYS because of the risk of exacerbating the psychosis with an increase in central dopaminergic tone. In addition, treatments for psychosis that antagonize the effects of dopaminergic medications may exacerbate the symptoms of PD.

5.6 Impulse Control/Compulsive Disorders

Patients treated with ONGENTYS can experience intense urges to gamble, increased sexual urges, intense urges to spend money, binge eating, and/or other intense urges, and the inability to control these urges while taking one or more dopaminergic therapies that increase central dopaminergic tone. In some cases, these urges were reported to have stopped when the dose was reduced, or the medication was discontinued. Because patients may not recognize these behaviors as abnormal, it is important for prescribers to specifically ask patients or their caregivers about the development of new or increased gambling urges, sexual urges, uncontrolled spending, or other urges while being treated with ONGENTYS.

In Study 1 and Study 2, impulse control disorders occurred in 1% of patients treated with ONGENTYS 50 mg, and in no patient who received placebo. Re-evaluate the patient’s current therapy(ies) for Parkinson’s disease and consider stopping ONGENTYS if a patient develops such urges while taking ONGENTYS.

Use with caution in Parkinson’s patients with suspected or diagnosed dopamine dysregulation syndrome.

5.7 Withdrawal-Emergent Hyperpyrexia and Confusion

A symptom complex resembling neuroleptic malignant syndrome (characterized by elevated temperature, muscular rigidity, altered consciousness, and autonomic instability), with no other obvious etiology, has been reported in association with rapid dose reduction, withdrawal of, or changes in drugs that increase central dopaminergic tone. In the controlled clinical studies of ONGENTYS, patients discontinued ONGENTYS treatment without dose tapering or gradual withdrawal. There were no reports of neuroleptic malignant syndrome in ONGENTYS controlled clinical studies. When discontinuing ONGENTYS, monitor patients and consider adjustment of other dopaminergic therapies as needed [see Dosage and Administration (2.3)].

6 ADVERSE REACTIONS

The following clinically significant adverse reactions are discussed in more detail in other sections of the labeling:

- Cardiovascular Effects with Concomitant Use of Drugs Metabolized by Catechol-O-Methyltransferase (COMT) [see Warnings and Precautions (5.1)]
- Falling Asleep During Activities of Daily Living and Somnolence [see Warnings and Precautions (5.2)]
- Hypotension/Syncope [see Warnings and Precautions (5.3)]
- Dyskinesia [see Warnings and Precautions (5.4)]
- Hallucinations and Psychosis [see Warnings and Precautions (5.5)]
- Impulse Control/Compulsive Disorders [see Warnings and Precautions (5.6)]
- Withdrawal-Emergent Hyperpyrexia and Confusion [see Warnings and Precautions (5.7)]

6.1 Clinical Trials Experience

Because clinical trials are conducted under widely varying conditions, adverse reaction rates observed in the clinical trials of a drug cannot be directly compared to rates in the clinical trials of another drug and may not reflect the rates observed in practice.

The safety of ONGENTYS was evaluated in 265 patients with Parkinson’s disease (PD) in two 14-15 week placebo- and active-controlled (Study 1) or placebo-controlled (Study 2) studies [see Clinical Studies (14)]. All patients were taking a stable dose of levodopa and a DOPA decarboxylase inhibitor, alone or in combination with other PD medications. In Study 1 and Study 2, the mean age of patients was 63.6 years, 59% of patients were male, and 89% of patients were Caucasian. At baseline, the mean duration of PD was 7.6 years.

Adverse Reactions Leading to Discontinuation of Treatment

In Study 1 and Study 2, a total of 8% of ONGENTYS 50 mg-treated patients and 6% of patients who received placebo discontinued due to adverse events. The most common adverse reaction leading to discontinuation was dyskinesia, reported in 3% of ONGENTYS 50 mg-treated patients and 0.4% of patients who received placebo.

Common Adverse Reactions

Adverse reactions that occurred in the pooled studies at an incidence of at least 2% and greater than placebo are presented in Table 1. The most common adverse reactions (incidence at least 4% and greater than placebo) were dyskinesia, constipation, blood creatine kinase increased, hypotension/syncope, and weight decreased.

Table 1: Adverse Reactions with an Incidence of at Least 2% in Patients Treated with ONGENTYS and Greater than on Placebo, in Pooled Study 1 and Study 2

Adverse Reactions | ONGENTYS 50 mg N=265 % | Placebo N=257 %
Nervous system disorders Dyskinesia Dizziness | 20 3 | 6 1
Gastrointestinal disorders Constipation Dry mouth | 6 3 | 2 1
Psychiatric disorders Hallucination^1 Insomnia | 3 3 | 1 2
Investigations Blood creatine kinase increased Weight decreased | 5 4 | 2 0
Vascular disorders Hypotension/syncope^2 Hypertension | 5 3 | 1 2

^1 Includes hallucinations, hallucinations visual, hallucinations auditory, and hallucinations mixed

^2 Includes hypotension, orthostatic hypotension, syncope, and presyncope

6.2 Postmarketing Experience

The following adverse reactions have been identified during postapproval use of ONGENTYS. Because these reactions are reported voluntarily from a population of uncertain size, it is not always possible to reliably estimate their frequency or establish causal relationship to drug exposure.

Injury, poisoning and procedural complications: Fall

Psychiatric disorder: Confusional state

7 DRUG INTERACTIONS

7.1 Non-Selective Monoamine Oxidase (MAO) Inhibitors

Both ONGENTYS and non-selective MAO inhibitors (e.g., phenelzine, isocarboxazid, and tranylcypromine) inhibit catecholamine metabolism, leading to increased levels of catecholamines. Concomitant use may increase the risk of possible arrhythmias, increased heart rate, and excessive changes in blood pressure.

Concomitant use of ONGENTYS with non-selective MAO inhibitors is contraindicated [see Contraindications (4)]. Selective MAO-B inhibitors can be used concomitantly with ONGENTYS.

7.2 Effect of ONGENTYS on Other Drugs

Drugs Metabolized by Catechol-O-Methyltransferase (COMT)

Concomitant use of ONGENTYS with drugs metabolized by COMT may affect the pharmacokinetics of those drugs, which may increase the risk of possible arrhythmias, increased heart rate, and excessive changes in blood pressure [see Warnings and Precautions (5.1)]. Drugs known to be metabolized by COMT should be administered with caution. Monitor for changes in heart rate, rhythm, and blood pressure in patients concomitantly treated with ONGENTYS and drugs metabolized by COMT [see Warnings and Precautions (5.1)].

8 USE IN SPECIFIC POPULATIONS

8.1 Pregnancy

Risk Summary

There are no adequate data on the developmental risk associated with use of ONGENTYS in pregnant women. In animal studies, oral administration of opicapone during pregnancy resulted in adverse effects on embryofetal development (increased incidence of fetal abnormalities) at clinically relevant plasma exposures in one of two species tested. In addition, opicapone is always given concomitantly with levodopa/carbidopa, which is known to cause developmental toxicity in rabbits (see Data).

The background risk of major birth defects and miscarriage in the U.S. general population is 2-4% and 15-20% of clinically recognized pregnancies, respectively. The background risk for major birth defects and miscarriage in patients with Parkinson’s disease is unknown.

Data

Animal Data

Oral administration of opicapone (0, 150, 375, or 1000 mg/kg/day) to pregnant rats throughout gestation resulted in no adverse effects on embryofetal development. Plasma exposure (AUC) at the highest dose tested (1000 mg/kg/day) was approximately 40 times that in humans at the recommended human dose (50 mg/day).

In pregnant rabbits, oral administration of opicapone (0, 100, 175, or 225 mg/kg/day) during the period of organogenesis resulted in increased incidence of structural abnormalities at all doses tested; maternal toxicity was observed at all but the lowest dose tested. A no-effect dose for adverse effects on embryofetal development was not identified. Plasma exposure (AUC) at the low-effect dose (100 mg/kg/day) was less than that in humans at the RHD.

Oral administration of opicapone (0, 150, 375, or 1000 mg/kg/day) throughout gestation and lactation resulted in no adverse effects on pre- and postnatal development; however, effects on neurobehavioral development in the offspring were not rigorously assessed. Plasma exposure (AUC) at the highest dose tested (1000 mg/kg/day) was approximately 40 times that in humans at the RHD.

Opicapone is always given concomitantly with levodopa/carbidopa, which is known to cause visceral and skeletal malformations in rabbits. The developmental toxicity of opicapone in combination with levodopa/carbidopa was not assessed in animals.

8.2 Lactation

Risk Summary

There are no data on the presence of opicapone in human milk, the effects on the breastfed infant, or the effects on milk production. In lactating rats, oral administration of opicapone resulted in levels of opicapone or metabolites in milk similar to those in maternal plasma. The developmental and health benefits of breastfeeding should be considered along with the mother’s clinical need for ONGENTYS and any potential adverse effects on the breastfed infant from ONGENTYS or from the underlying maternal condition.

8.4 Pediatric Use

Safety and effectiveness in pediatric patients have not been established.

8.5 Geriatric Use

No dose adjustment is required for elderly patients. Of the total number of patients who received ONGENTYS 50 mg in Study 1 and Study 2, 52% of patients were 65 years and older. No overall differences in safety and effectiveness were observed between these patients and younger patients, but greater sensitivity to adverse reactions of some older individuals cannot be ruled out.

8.6 Renal Impairment

The renal route of elimination plays a minor role in the clearance of opicapone [see Clinical Pharmacology (12.3)]. Avoid use of ONGENTYS in patients with end-stage renal disease (ESRD) (CLcr <15 mL/min). No dosage adjustment is required for patients with mild, moderate, or severe renal impairment. However, because of a potential for increased exposure, monitor patients with severe renal impairment for adverse reactions and discontinue ONGENTYS if tolerability issues arise.

8.7 Hepatic Impairment

Opicapone exposure is increased in patients with hepatic impairment [see Clinical Pharmacology (12.3)]. Avoid use of ONGENTYS in patients with severe (Child-Pugh C) hepatic impairment. Dosage adjustment is recommended for patients with moderate (Child-Pugh B) hepatic impairment [see Dosage and Administration (2.2)]. No dosage adjustment is required in patients with mild (Child-Pugh A) hepatic impairment.

10 OVERDOSAGE

No specific antidotes for ONGENTYS are known. As a general measure, removal of ONGENTYS by gastric lavage and/or inactivation by administering activated charcoal should be considered. In managing overdose, provide supportive care, including close medical supervision and monitoring, and consider the possibility of multiple drug involvement. If an over-exposure occurs, call your poison control center at 1-800-222-1222 or www.poison.org.

11 DESCRIPTION

ONGENTYS contains opicapone, a peripheral, selective and reversible catechol-O-methyltransferase (COMT) inhibitor. The chemical name of opicapone is 2,5-dichloro-3-(5-(3,4-dihydroxy-5-nitrophenyl)-1,2,4-oxadiazol-3-yl)-4,6-dimethylpyridine-1-oxide with the following structure:

The opicapone molecular formula is C15H10Cl2N4O6; and its molecular weight is 413.17.

Opicapone is a yellow powder/crystalline solid with limited aqueous solubility.

ONGENTYS capsules are intended for oral administration. Each capsule contains 25 mg or 50 mg of opicapone. ONGENTYS also contains the following inactive ingredients: lactose, magnesium stearate, pregelatinized starch, and sodium starch glycolate. The capsule shells contain: FD&C Blue#2, FD&C Red#3, gelatin, and titanium dioxide.

12 CLINICAL PHARMACOLOGY

12.1 Mechanism of Action

Opicapone is a selective and reversible inhibitor of catechol-O-methyltransferase (COMT).

COMT catalyzes the transfer of the methyl group of S-adenosyl-L-methionine to the phenolic group of substrates that contain a catechol structure. Physiological substrates of COMT include DOPA, catecholamines (dopamine, norepinephrine, and epinephrine), and their hydroxylated metabolites. When decarboxylation of levodopa is prevented by carbidopa, COMT becomes the major metabolizing enzyme for levodopa, catalyzing its metabolism to 3-methoxy-4-hydroxy-L-phenylalanine (3-OMD).

12.2 Pharmacodynamics

COMT Activity

Once-daily administration of ONGENTYS 50 mg caused inhibition of COMT activity in erythrocytes; the maximal inhibition seen was 84% and was maintained >65% over a 24-hour dosing interval in patients with Parkinson’s disease. Following termination of treatment, COMT inhibition slowly returns to baseline levels, with >35% inhibition still observed 5 days after the last dose.

Effects on Levodopa

Peak (Cmax) and overall levodopa exposure (AUC) increased by 43-44% and 62-94%, respectively, in PD patients following once-daily administration of ONGENTYS at bedtime with levodopa/carbidopa administered every three or every four hours, as compared to after administration of levodopa/carbidopa alone.

Cardiac Electrophysiology

At a dose 16 times the recommended dosage, ONGENTYS does not prolong the QT interval to any clinically relevant extent.

12.3 Pharmacokinetics

Opicapone demonstrates dose-proportional pharmacokinetics over a 25 mg (0.5 times the recommended dosage) to 50 mg dose range. The pharmacokinetics of opicapone are similar in both PD patients and healthy subjects.

Absorption

After single-dose administration of ONGENTYS 50 mg, the median (range) plasma Tmax value was 2.0 (1.0-4.0) hours.

Effect of Food

Following a moderate fat/moderate calorie meal, the mean peak plasma concentration (Cmax) for opicapone decreased 62%, the mean overall plasma exposure (AUC) decreased 31%, and the Tmax was delayed by 4 hours. In Study 1, ONGENTYS was administered without regard to food. In Study 2, ONGENTYS administration and food consumption were separated by 1 hour [see Dosage and Administration (2.1), Clinical Studies (14)].

Distribution

Opicapone is highly bound to plasma proteins (>99%), which is independent of concentration.

Elimination

The mean elimination half-life of opicapone is 1 to 2 hours.

Metabolism

Sulphation is the primary metabolic pathway of opicapone, based on clinical studies and in vitro assessments. Other metabolic pathways include glucuronidation, methylation (by COMT), reduction, and glutathione conjugation.

Excretion

After administration of a single dose of radiolabeled opicapone 100 mg (2 times the recommended dosage) to healthy subjects, approximately 70% of the dose was recovered in feces (22% as unchanged), 20% in expired air, and 5% in urine (<1% as unchanged).

Specific Populations

No clinically significant differences in the pharmacokinetics of opicapone were observed based on age (i.e., 18 to 40 years of age and ≥ 65 years of age), sex, or race/ethnicity (i.e., Japanese, Caucasian, Asian, and Black).

Renal Impairment

Based on population pharmacokinetic analyses, no clinically significant differences in the pharmacokinetics of opicapone were observed in patients with mild or moderate renal impairment (CLcr 30-89 mL/min using the Cockcroft-Gault equation) relative to those with normal renal function (CLcr >90 mL/min). Patients with severe renal impairment or ESRD (CLcr <30 mL/min) have not been studied [see Use in Specific Populations (8.6)].

Hepatic Impairment

The single-dose pharmacokinetics of opicapone was evaluated in subjects with mild (Child-Pugh: A) and moderate (Child-Pugh: B) hepatic impairment. In subjects with mild hepatic impairment, the mean overall opicapone plasma exposure (AUC) increased by 35%, which is not expected to be clinically significant. In subjects with moderate hepatic impairment, the mean overall opicapone plasma exposure (AUC) increased by 84%. Dosage adjustment for ONGENTYS is required in subjects with moderate hepatic impairment [see Dosage and Administration (2.2)]. ONGENTYS has not been studied in patients with severe hepatic impairment (Child-Pugh: C) [see Use in Specific Populations (8.7)].

Drug Interaction Studies

Clinical Studies

No clinically significant differences in the pharmacokinetics of opicapone were observed when administered concomitantly with quinidine (index substrate of P-gp [MDR1]), acetaminophen, or rasagiline.

No clinically significant differences in the pharmacokinetics of the following drugs were observed when administered concomitantly with opicapone: S-warfarin (index substrate of CYP2C9), R-Warfarin (substrate of CYP1A2 and CYP3A4), or repaglinide (index substrate of CYP2C8 and OATP1B1).

No clinically significant differences in the pharmacokinetics of the following drugs for the treatment of Parkinson’s disease were observed when administered concomitantly with opicapone: rasagiline, selegiline, pramipexole, ropinirole, or amantadine.

In Vitro Studies

Opicapone does not affect protein binding of warfarin, diazepam, digoxin, or tolbutamide, in vitro.

CYP Enzymes: Opicapone is not an inhibitor or inducer of major CYPs.

Transporter Systems: Opicapone is a substrate of P-gp (MDR1) (see Clinical Studies), BCRP, MRP2, OATP1B3, and OATP2B1. No clinically significant transporter mediated interaction is expected for opicapone. Opicapone is not an inhibitor of P-gp (MDR1), BCRP, OAT1, OAT3, OCT1, OCT2, OATP1B3, BSEP, MATE1, or MATE2-K.

13 NONCLINICAL TOXICOLOGY

13.1 Carcinogenesis, Mutagenesis, Impairment of Fertility

Carcinogenesis

No increase in tumors was observed when opicapone was administered orally to mice (0, 100, 375, or 750 mg/kg/day) for up to 2 years (84-93 weeks at the high dose). The highest dose tested is approximately 70 times the recommended dose (RHD) in humans (50 mg/day) on a body surface area (mg/m^2) basis.

No increase in tumors was observed when opicapone was administered orally to rats (0, 100, 500, or 1000 mg/kg/day) for 2 years. Plasma exposure (AUC) at the highest dose tested is approximately 24 times that in humans at the RHD (50 mg/day).

Mutagenesis

Opicapone was negative in in vitro (bacterial reverse mutation test (Ames), chromosomal aberrations in human peripheral blood lymphocytes) and in in vivo (rat bone marrow micronucleus) assays.

Impairment of Fertility

In male and female rats, oral administration of opicapone (0, 100, 500, or 1000 mg/kg/day) prior to and during mating and continuing in females to gestation day 6, resulted in no adverse effects on fertility or general reproductive performance. Plasma exposure (AUC) at the highest dose tested is approximately 40 times that in humans at the RHD.

14 CLINICAL STUDIES

The efficacy of ONGENTYS for the adjunctive treatment to levodopa/carbidopa in patients with Parkinson’s disease (PD) experiencing “off” episodes was evaluated in two double-blind, randomized, parallel-group, placebo- and active-controlled (Study 1, NCT01568073), or placebo-controlled (Study 2, NCT01227655) studies of 14-15 week duration. All patients were treated with levodopa/ DOPA decarboxylase inhibitor (DDCI) (alone or in combination with other PD medications). The double-blind period for each study began with a period for levodopa/DDCI dose adjustment (up to 3 weeks), followed by a stable maintenance period of 12 weeks.

Study 1

In Study 1, patients (n=600) were randomized to treatment with one of 3 doses of ONGENTYS. The intention to treat (ITT) population included patients treated with ONGENTYS 50 mg once daily (n=115) or placebo (n=120). Baseline demographic characteristics were similar across all treatment groups: approximately 60% of patients were male, mean age was 64 years, and all patients were Caucasian. Baseline PD characteristics in the treatment groups were: mean duration of PD of 7 years for ONGENTYS 50 mg compared to 7.7 years for placebo, and mean onset of motor fluctuations of 2.2 years prior to study enrollment. Eighty-two percent of patients in both groups used concomitant PD medications in addition to levodopa; the most commonly used were dopamine agonists (68%), amantadine (23%), MAO-B inhibitors (20%), and anticholinergics (5%).

The primary efficacy endpoint was the change in mean absolute OFF-time based on 24-hour patient diaries completed 3 days prior to each of the scheduled visits. ONGENTYS 50 mg significantly reduced mean absolute OFF-time compared to placebo (Table 2).

Table 2: Study 1 - Absolute OFF-time (Hours) Change from Baseline to Endpoint

 | N | Baseline Mean (SE) | LS Mean Change from Baseline (SE) | Placebo-subtracted Difference (95% CI) | Adjusted p-valuea
Placebo | 120 | 6.17 hours (0.162) | -0.93 (0.223) | -- | --
ONGENTYS 50 mg | 115 | 6.20 hours (0.166) | -1.95 (0.233) | -1.01 (-1.620, -0.407) | p=0.002
CI=confidence interval; LS =least squares; N=total number of patients; SE=standard error.
a Adjusted p values were calculated using a gatekeeping procedure controlling for multiplicity.

ON-time without troublesome dyskinesia was a secondary efficacy endpoint in Study 1 (Table 3).

Table 3: Study 1 - Absolute ON-time Without Troublesome Dyskinesia (Hours) Change from Baseline to Endpoint

 | N | Baseline Mean (SE) | LS Mean Change from Baseline (SE) | Placebo-subtracted Difference (95% CI) | Nominal p-value a
Placebo | 120 | 9.61 (0.191) | 0.75 (0.237) | -- | --
ONGENTYS 50 mg | 115 | 9.54 (0.183) | 1.84 (0.247) | 1.08 (0.440, 1.728) | p=0.001
CI=confidence interval; LS =least squares; N=total number of patients; SE=standard error.
a Unadjusted p-value.

Study 2

In Study 2, patients (n=427) were randomized to treatment with either one of two doses of ONGENTYS once daily (n=283) or placebo (n=144). The intention to treat (ITT) study population included patients treated with ONGENTYS 50 mg once daily (n=147) or placebo (n=135). Baseline demographic characteristics (ONGENTYS 50 mg vs. placebo) were: mean age (66 years vs. 62 years), male (61% vs. 53%), Caucasian (78% vs. 66%) and Asian (21% vs. 31%). Baseline PD characteristics were generally similar across treatment groups with a mean duration of PD of 8.2 years, and a mean onset of motor fluctuations of 3.2 years prior to study enrollment. Eighty-five percent of patients treated with ONGENTYS 50 mg compared to 81% of patients who received placebo used concomitant PD medications in addition to levodopa; the most commonly used were dopamine agonists (70%), amantadine (21%), MAO-B inhibitors (20%), and anticholinergics (12%).

The primary efficacy endpoint was the change in mean absolute OFF-time based on 24-hour patient diaries completed 3 days prior to each of the scheduled visits. ONGENTYS 50 mg significantly reduced mean absolute OFF-time compared to placebo (Table 4).

Table 4: Study 2 - Absolute OFF-time (Hours) Change from Baseline to Endpoint

 | N | Baseline Mean (SE) | LS Mean Change from Baseline (SE) | Placebo-subtracted Difference (95% CI) | Adjusted p-valuea
Placebo | 135 | 6.12 (0.200) | -1.07 (0.239) | -- | --
ONGENTYS 50 mg | 147 | 6.32 (0.183) | -1.98 (0.230) | -0.91 (-1.523, -0.287) | p=0.008
CI=confidence interval; LS =least squares; N=total number of patients; SE=standard error.
a Adjusted p values were calculated using Dunnett's alpha level adjustment to control for multiplicity.

ON-time without troublesome dyskinesia was a secondary efficacy endpoint in Study 2 (Table 5).

Table 5: Study 2 - Absolute ON-time Without Troublesome Dyskinesia (Hours) Change from Baseline to Endpoint

 | N | Baseline Mean (SE) | LS Mean Change from Baseline (SE) | Placebo-subtracted Difference (95% CI) | Nominal p-value
Placebo | 135 | 9.61 (0.206) | 0.80 (0.256) | -- | --
ONGENTYS 50 mg | 147 | 9.37 (0.183) | 1.43 (0.247) | 0.62 (-0.039, 1.287) | p=0.065 (NS*)
CI=confidence interval; LS =least squares; N=total number of patients; SE=standard error.
*= not statistically significant.

16 HOW SUPPLIED/STORAGE AND HANDLING

16.1 How Supplied

ONGENTYS (opicapone) capsules are available as:

• 50 mg hard gelatin capsules, Size 1; dark blue opaque cap and dark pink opaque body; axially printed with “OPC” over “50” in white ink, on both the cap and body

- Bottle of 30 with child-resistant closure: NDC 64896-403-01

• 25 mg hard gelatin capsules, Size 1; light blue opaque cap and light pink opaque body; axially printed with “OPC” over “25” in blue ink, on both the cap and body

- Bottle of 30 with child-resistant closure: NDC 64896-402-01

16.2 Storage and Handling

Store at a temperature below 30°C (86°F).

17 PATIENT COUNSELING INFORMATION

Advise the patient to read the FDA-approved patient labeling (Patient Information).

Administration

Instruct patients and/or caregivers that ONGENTYS capsules should be taken at bedtime. Inform patients to not eat food for 1 hour before and for at least 1 hour after intake of ONGENTYS [see Dosage and Administration (2.1)].

Concomitant Medications

Certain medications can cause an interaction with ONGENTYS. Advise patients and/or caregivers to inform their healthcare provider of all the medicines the patient is taking, including over-the-counter medicines, dietary supplements, and herbal products [see Warnings and Precautions (5.1) and Drug Interactions (7)].

Falling Asleep During Activities of Daily Living

Advise patients and/or caregivers that somnolence has been reported with ONGENTYS. Patients treated with dopaminergic medications have reported falling asleep while engaged in activities of daily living. These adverse reactions may affect some patients’ ability to drive and operate machinery safely [see Warnings and Precautions (5.2)].

Hypotension/Syncope

Advise patients that ONGENTYS may cause hypotension or syncope [see Warnings and Precautions (5.3)].

Dyskinesia

Advise patients that ONGENTYS may cause dyskinesia or exacerbate pre-existing dyskinesia [see Warnings and Precautions (5.4)].

Hallucinations and Psychosis

Advise patients that ONGENTYS may cause hallucinations, delusions, or aggressive behavior and they should report any of these adverse reactions to their healthcare provider [see Warnings and Precautions (5.5)].

Impulse Control/Compulsive Disorders

Inform patients of the potential for experiencing intense urges to gamble, increased sexual urges, intense urges to spend money, binge eating, and other intense urges and the inability to control these urges while taking ONGENTYS and one or more medications that increase central dopaminergic tone that are generally used for the treatment of PD. Advise patients that they should report any of these adverse reactions to their healthcare provider [see Warnings and Precautions (5.6)].

Withdrawal-Emergent Hyperpyrexia and Confusion

Advise patients to contact their healthcare provider before stopping ONGENTYS. Tell patients to inform their healthcare provider if they develop symptoms such as fever, confusion, or severe muscle stiffness after stopping ONGENTYS [see Warnings and Precautions (5.7)].

For further information on ONGENTYS, call 1-877-835-5472 or visit www.ongentys.com

Distributed by:
Amneal Specialty, a division of Amneal Pharmaceuticals LLC
Bridgewater, NJ 08807

Rev. 10-2025-02

Under license from BIAL-Portela & Ca, S.A.

ONGENTYS is a registered trademark of BIAL-Portela & Ca, S.A.

PATIENT INFORMATION

ONGENTYS® (on-JEN-tis)
(opicapone) capsules

What is ONGENTYS?
ONGENTYS is a prescription medicine used with levodopa and carbidopa in people with Parkinson’s disease (PD) who are having “OFF” episodes.
It is not known if ONGENTYS is safe and effective in children.

Do not take ONGENTYS if you:

- take a type of medicine called a non-selective monoamine-oxidase (MAO) inhibitor, such as phenelzine, isocarboxazid, or tranylcypromine. Ask your healthcare provider or pharmacist if you are taking a non-selective MAO inhibitor.
- have a tumor that secretes hormones known as catecholamines. These tumors include pheochromocytoma (a type of adrenal gland tumor) and paraganglioma.

Before taking ONGENTYS, tell your healthcare provider about all of your medical conditions, including if you:

- have daytime sleepiness from a sleep disorder, have unexpected or unpredictable periods of sleep or sleepiness, take a medicine to help you sleep, or take any medicine that makes you feel sleepy.
- have or have had intense urges or unusual behaviors, including gambling, increased sex drive, binge eating, or compulsive shopping.
- have a history of uncontrolled sudden movements (dyskinesia).
- have or have had hallucinations or psychosis.
- have liver problems.
- have kidney problems.
- are pregnant or plan to become pregnant. It is not known if ONGENTYS will harm your unborn baby.
- are breastfeeding or plan to breastfeed. It is not known if ONGENTYS passes into breast milk. You and your healthcare provider should decide the best way to feed your baby if you take ONGENTYS.

Tell your healthcare provider about all the medicines you take, including prescription and over-the-counter medicines, vitamins, and herbal supplements. Especially tell your healthcare provider if you take nonselective MAO inhibitors (such as phenelzine, tranylcypromine, and isocarboxazid) or catecholamine medicines (such as isoproterenol, epinephrine, norepinephrine, dopamine, and dobutamine), regardless of how you take the medicine (by mouth, inhaled, or by injection).
ONGENTYS and other medicines may affect each other causing side effects. ONGENTYS may affect the way other medicines work, and other medicines may affect how ONGENTYS works.
Know the medicines you take. Keep a list of them to show your healthcare provider and pharmacist when you get a new medicine.

How should I take ONGENTYS?
• Take ONGENTYS exactly as your healthcare provider tells you to.
• ONGENTYS should be taken 1 time each day at bedtime.
• Do not eat 1 hour before taking ONGENTYS and do not eat for at least 1 hour after taking ONGENTYS.
• If you miss a dose, take your usual dose of ONGENTYS on the next day at bedtime.
• Do not stop taking ONGENTYS or change your dose before talking to your healthcare provider.
○ Your dose of other Parkinson’s disease medicines may change when stopping ONGENTYS. Tell your healthcare provider if you have symptoms of withdrawal such as fever, confusion, or severe muscle stiffness.
• If you take too much ONGENTYS, call your healthcare provider or Poison Control Center at 1-800-222-1222, or go to the nearest hospital emergency room right away.

What should I avoid while taking ONGENTYS?

- Do not drive, operate machinery, or do other dangerous activities until you know how ONGENTYS affects you.

What are the possible side effects of ONGENTYS?
ONGENTYS may cause serious side effects, including:

- Falling asleep during normal activities. You may suddenly fall asleep while doing normal activities such as driving a car, talking or eating while taking ONGENTYS or other medicines used to treat Parkinson’s disease, without being drowsy or without warning. This may result in having accidents. Your chances of falling asleep while doing normal activities while taking ONGENTYS are higher if you take other medicines that cause drowsiness.
- Low blood pressure or dizziness. Low blood pressure, dizziness, light headedness, or fainting can happen with ONGENTYS. Tell your healthcare provider if you become dizzy, lightheaded, or faint while taking ONGENTYS.
- Uncontrolled sudden movements (dyskinesia). ONGENTYS may cause uncontrolled sudden movements or make such movements you already have worse or happen more often. Tell your healthcare provider if this happens.
- Seeing, hearing, believing, or feeling things that are not real or not true. Taking ONGENTYS may cause seeing, hearing, or feeling things that are not real (hallucinations), believing things that are not real (delusions), or aggressive behavior. Tell your healthcare provider if you have any of these changes in your behavior.
- Unusual urges (impulse control and compulsive disorders). Some people taking ONGENTYS may get urges to behave in a way unusual for them. Examples of this are unusual urges to gamble, increased sexual urges, strong urges to spend money, binge eating, and the inability to control these urges. If you or your family notice that you are developing any unusual behaviors, talk to your healthcare provider.

Tell your healthcare provider if you experience any of these side effects.
The most common side effects of ONGENTYS include:

- uncontrolled sudden movements (dyskinesia)
- constipation
- increase in a certain enzyme called blood creatine kinase

- low blood pressure
- weight loss

These are not all of the possible side effects of ONGENTYS. Call your healthcare provider for medical advice about side effects. You may report side effects to FDA at 1-800-FDA-1088.

How should I store ONGENTYS?

- Store ONGENTYS at a temperature below 86°F (30°C).
- Keep ONGENTYS and all medicines out of the reach of children.

General information about the safe and effective use of ONGENTYS.
Medicines are sometimes prescribed for purposes other than those listed in a Patient Information leaflet. Do not use ONGENTYS for a condition for which it was not prescribed. Do not give ONGENTYS to other people, even if they have the same symptoms that you have. It may harm them. You can ask your pharmacist or healthcare provider for information about ONGENTYS that is written for health professionals.

What are the ingredients in ONGENTYS?
Active ingredient: opicapone
Inactive ingredients: lactose, magnesium stearate, pregelatinized starch, and sodium starch glycolate. The capsule shells contain: FD&C Blue#2, FD&C Red#3, gelatin, and titanium dioxide.

Distributed by:

Amneal Specialty, a division of Amneal Pharmaceuticals LLC

Bridgewater, NJ 08807

Under license from BIAL-Portela & Ca, S.A. ONGENTYS is a registered trademark of BIAL-Portela & Ca, S.A.

For more information, go to www.ongentys.com or call 1-877-835-5472.

This Patient Information has been approved by the U.S. Food and Drug Administration Rev. 12-2023-00

PRINCIPAL DISPLAY PANEL

NDC 64896-402-01

Ongentys®

(opicapone) capsules

25 mg

30 Capsules

Rx only

PRINCIPAL DISPLAY PANEL

NDC 64896-403-01

Ongentys®

(opicapone) capsules

50 mg

30 Capsules

Rx only